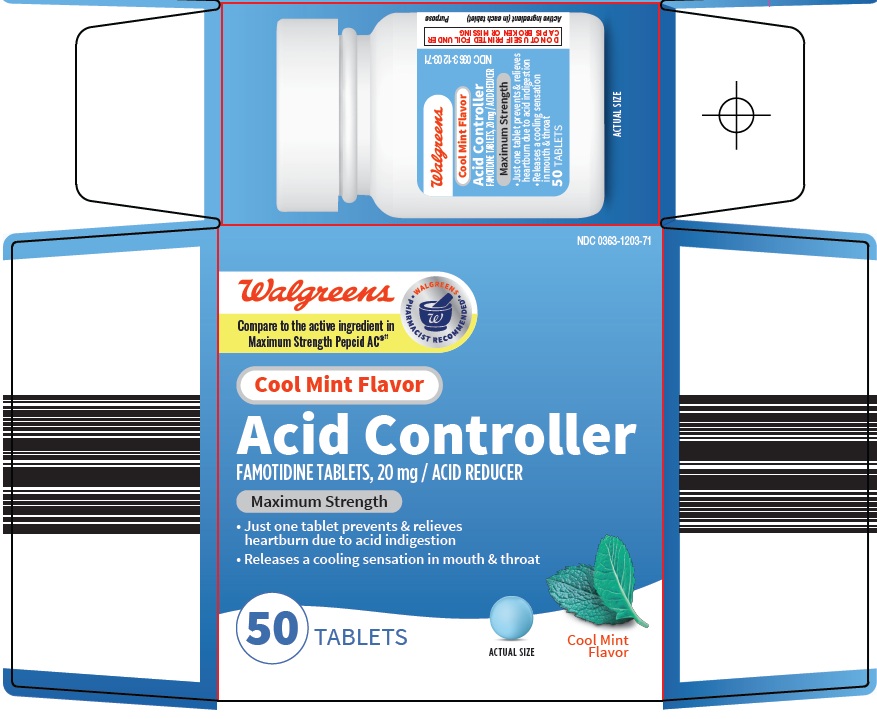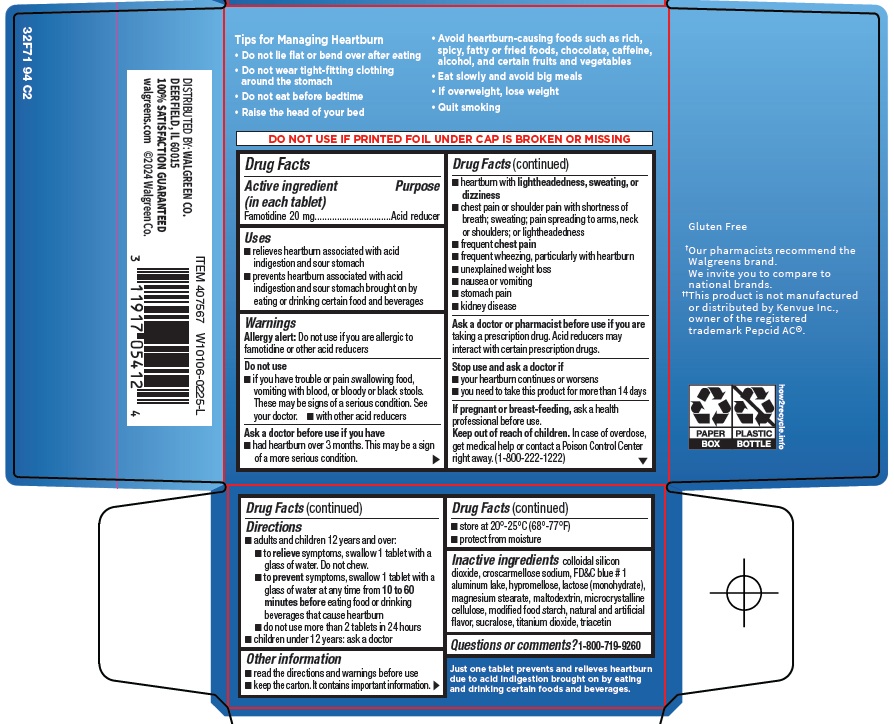 DRUG LABEL: acid controller
NDC: 0363-1203 | Form: TABLET, FILM COATED
Manufacturer: Walgreen Company
Category: otc | Type: HUMAN OTC DRUG LABEL
Date: 20260228

ACTIVE INGREDIENTS: FAMOTIDINE 20 mg/1 1
INACTIVE INGREDIENTS: SILICON DIOXIDE; CROSCARMELLOSE SODIUM; FD&C BLUE NO. 1 ALUMINUM LAKE; HYPROMELLOSE, UNSPECIFIED; LACTOSE MONOHYDRATE; MAGNESIUM STEARATE; MALTODEXTRIN; MICROCRYSTALLINE CELLULOSE; SUCRALOSE; TITANIUM DIOXIDE; TRIACETIN

Walgreen Co. Acid Controller Drug Facts

Active ingredient (in each tablet)

Famotidine 20 mg

Purpose

Acid reducer

Uses

- relieves heartburn associated with acid indigestion and sour stomach
- prevents heartburn associated with acid indigestion and sour stomach brought on by eating or drinking certain food and beverages

Warnings

Allergy alert: Do not use if you are allergic to famotidine or other acid reducers

Do not use

- if you have trouble or pain swallowing food, vomiting with blood, or bloody or black stools. These may be signs of a serious condition. See your doctor.
- with other acid reducers

Ask a doctor before use if you have

- had heartburn over 3 months. This may be a sign of a more serious condition.
- heartburn with lightheadedness, sweating, or dizziness
- chest pain or shoulder pain with shortness of breath; sweating; pain spreading to arms, neck or shoulders; or lightheadedness
- frequent chest pain
- frequent wheezing, particularly with heartburn
- unexplained weight loss
- nausea or vomiting
- stomach pain
- kidney disease

Ask a doctor or pharmacist before use if you are

taking a prescription drug. Acid reducers may interact with certain prescription drugs.

Stop use and ask a doctor if

- your heartburn continues or worsens
- you need to take this product for more than 14 days

If pregnant or breast-feeding,

ask a health professional before use.

Keep out of reach of children.

In case of overdose, get medical help or contact a Poison Control Center right away. (1-800-222-1222)

Directions

- adults and children 12 years and over:
- to relieve symptoms, swallow 1 tablet with a glass of water. Do not chew.
- to prevent symptoms, swallow 1 tablet with a glass of water at any time from 10 to 60 minutes before eating food or drinking beverages that cause heartburn
- do not use more than 2 tablets in 24 hours
- children under 12 years: ask a doctor

Other information

- read the directions and warnings before use
- keep the carton. It contains important information.
- store at 20˚-25˚C (68˚-77˚F)
- protect from moisture

Inactive ingredients

colloidal silicon dioxide, croscarmellose sodium, FD&C blue #1 aluminum lake, hypromellose, lactose (monohydrate), magnesium stearate, maltodextrin, microcrystalline cellulose, modified food starch, natural and artificial flavor, sucralose, titanium dioxide, triacetin

Questions or comments?

1-800-719-9260

Package/Label Principal Display Panel

Walgreens

WALGREENS PHARMACIST RECOMMENDED

Compare to the active ingredient in Maximum Strength Pepcid® AC

Cool Mint Flavor

Acid Controller

FAMOTIDINE TABLETS, 20 mg / ACID REDUCER

Maximum Strength

• Just one tablet prevents & relieves heartburn due to acid indigestion

• Releases a cooling sensation in mouth & throat

50 TABLETS

ACTUAL SIZE

Cool Mint Flavor